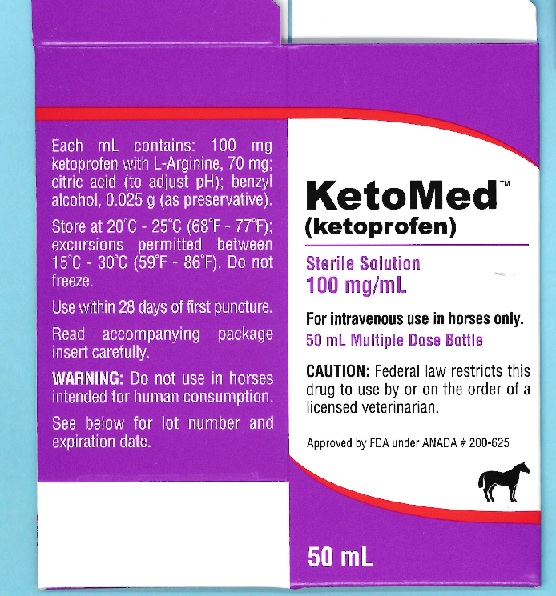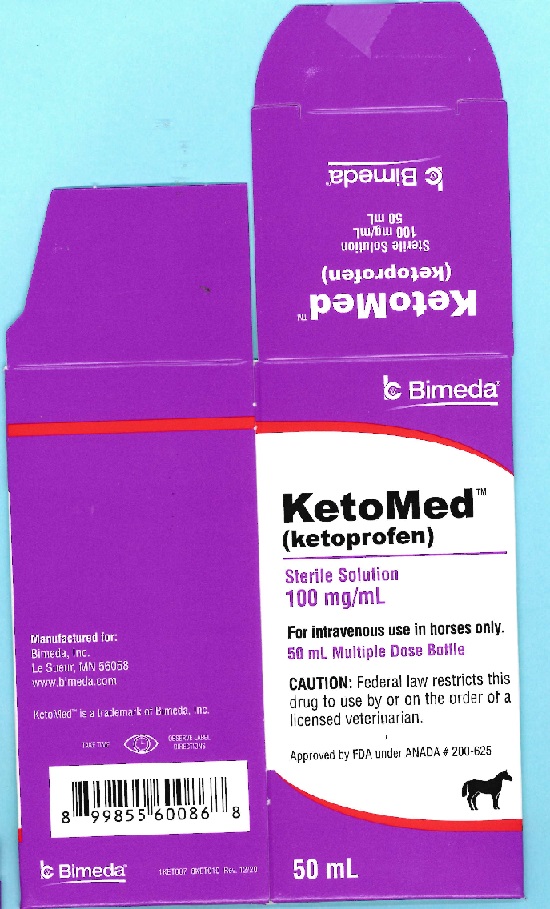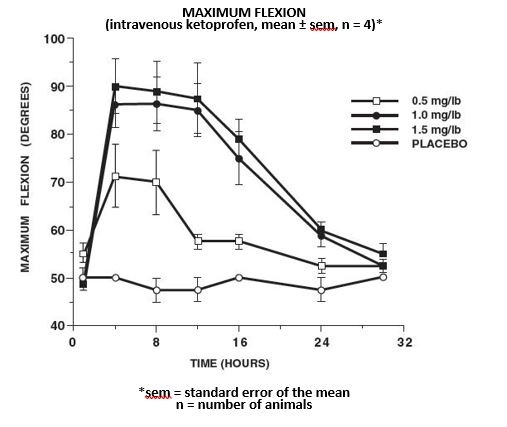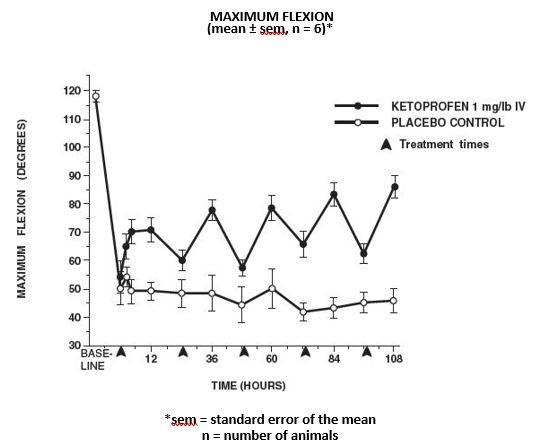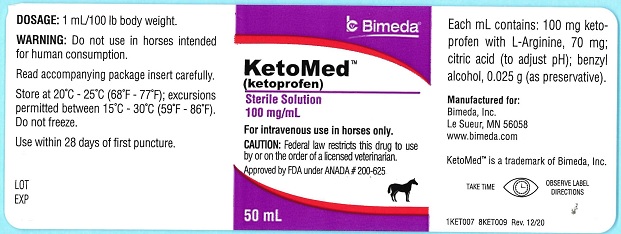 DRUG LABEL: KetoMed
NDC: 61133-4007 | Form: INJECTION, SOLUTION
Manufacturer: Bimeda, Inc.
Category: animal | Type: PRESCRIPTION ANIMAL DRUG LABEL
Date: 20241030

ACTIVE INGREDIENTS: KETOPROFEN 100 mg/1 mL
INACTIVE INGREDIENTS: ARGININE 70 mg/1 mL; CITRIC ACID MONOHYDRATE; BENZYL ALCOHOL

KetoMedTM

KetoMedTM
(ketoprofen)

Sterile Solution, 100 mg/mL

For intravenous use in horses only.

CAUTION

Federal law restricts this drug to use by or on the order of a licensed veterinarian.

DESCRIPTION

Ketoprofen is a non-steroidal anti-inflammatory agent of the propionic acid class that includes ibuprofen, naproxen, and fenoprofen. Each mL of KetoMed (ketoprofen) contains 100 mg of ketoprofen in an aqueous formulation containing: L-Arginine, 70 mg; citric acid (to adjust pH); benzyl alcohol, 0.025 g (as preservative).
It is packaged in a multiple dose bottle.

PHARMACOLOGY
KetoMed is a non-narcotic, non-steroidal anti-inflammatory agent with analgesic and antipyretic properties.

In horses, intravenous dosages of ketoprofen ranging from 0.5 to 1.5 mg/lb resulted in dosage dependent anti-inflammatory effects in the chronic adjuvant carpitis model as depicted in the following graph.

Additional studies using the same model in horses have shown that the effects of ketoprofen are maximal by 12 hours and still measurable at 24 hours after each dosage as depicted in the following graph.

TOXICITY
Horses were found to tolerate ketoprofen given intravenously at dosages of 0, 1, 3 and 5 mg/lb once daily for 15 consecutive days (up to five times the recommended dosage for three times the usual duration) with no evidence of toxic effects. In clinical studies, intravenous injection of 1 mg/lb/day for five days resulted in no injection site irritation or other side effects.

At 15-fold overdose (15 mg/lb/day) for five days one of two horses developed severe laminitis, but no gross lesions or histologic changes were observed. The toxic effects observed in the horses given a 25-fold overdose (25 mg/lb/day) for five days included inappetence, depression, icterus, abdominal swelling and postmortem findings of gastritis, nephritis and hepatitis.

INDICATIONS AND USAGE

INDICATION

KetoMed(ketoprofen) is recommended for the alleviation of inflammation and pain associated with musculoskeletal disorders in the horse.

DOSAGE AND ADMINISTRATION

The recommended dosage is 1 mg/lb (1 mL/100 lbs) of body weight once daily. Treatment is administered by intravenous injection and may be repeated for up to five days. Onset of activity is within two hours with peak response by 12 hours.

CONTRAINDICATIONS

There are no known contraindications to this drug when used as directed. Intra-arterial injection should be avoided. Do not use in a horse if it has previously shown hypersensitivity to ketoprofen.

CAUTION

This product should not be used in breeding animals since the effects of KetoMed on fertility, pregnancy or fetal health in horses have not been determined.

PRECAUTIONS

Studies to determine activity of KetoMed when administered concomitantly with other drugs have not been conducted. Drug compatibility should be monitored closely in patients requiring
adjunctive therapy.

WARNING

Do not use in horses intended for human consumption.

SIDE EFFECTS

During investigational studies, no significant side effects were reported.

To report suspected adverse drug events, for technical assistance, or to obtain a copy of the Safety Data Sheet (SDS), contact Bimeda, Inc. at 1-888-524-6332. For additional information about adverse drug experience reporting for animal drugs, contact FDA at 1-888-FDA-VETS or online at www.fda.gov/reportanimalae.

HOW SUPPLIED

KetoMed (ketoprofen) Solution 100 mg/mL is available in 50 mL and 100 mL multidose bottles.

STORAGE AND HANDLING

Store at 20°C - 25°C (68°F- 77°F); excursions permitted between 15°C - 30°C (59°F - 86°F). Do not freeze.

Use within 28 days of first puncture.

Approved by FDA under ANADA # 200-625
Manufactured for:
Bimeda, Inc.

Le Sueur, MN 56058

www.bimeda.com

12/20